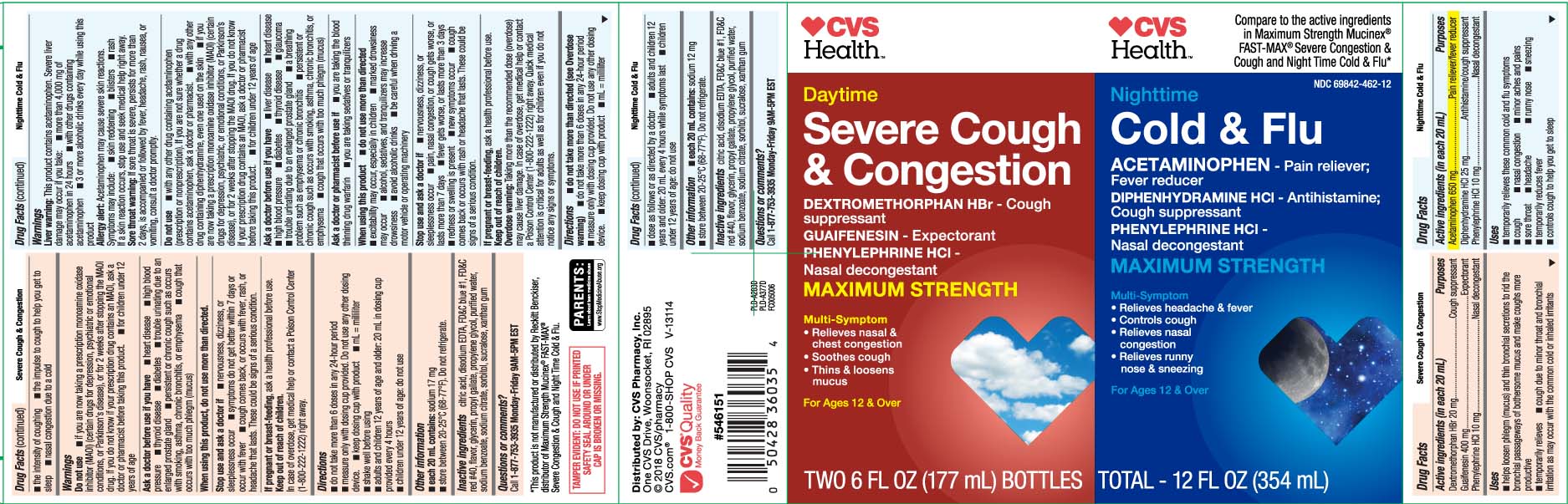 DRUG LABEL: Daytime Mucus Relief Severe Congestion and Cough and Nighttime Cold and Flu
NDC: 69842-462 | Form: KIT | Route: ORAL
Manufacturer: CVS Pharmacy
Category: otc | Type: HUMAN OTC DRUG LABEL
Date: 20250701

ACTIVE INGREDIENTS: DEXTROMETHORPHAN HYDROBROMIDE 20 mg/20 mL; GUAIFENESIN 400 mg/20 mL; PHENYLEPHRINE HYDROCHLORIDE 10 mg/20 mL; ACETAMINOPHEN 650 mg/20 mL; DIPHENHYDRAMINE HYDROCHLORIDE 25 mg/20 mL; PHENYLEPHRINE HYDROCHLORIDE 10 mg/20 mL
INACTIVE INGREDIENTS: ANHYDROUS CITRIC ACID; EDETATE DISODIUM; FD&C RED NO. 40; PROPYLENE GLYCOL; WATER; TRISODIUM CITRATE DIHYDRATE; FD&C BLUE NO. 1; GLYCERIN; PROPYL GALLATE; SODIUM BENZOATE; SORBITOL; SUCRALOSE; XANTHAN GUM; ANHYDROUS CITRIC ACID; EDETATE DISODIUM; FD&C BLUE NO. 1; FD&C RED NO. 40; PROPYLENE GLYCOL; WATER; SODIUM BENZOATE; TRISODIUM CITRATE DIHYDRATE; GLYCERIN; PROPYL GALLATE; SORBITOL; SUCRALOSE; XANTHAN GUM

Drug Facts

Active ingredients for Day Time (in each 20 mL)

Dextromethorphan HBr 20 mg

Guaifenesin 400 mg

Phenylephrine HCl 10 mg

Active ingredients for Night Time (in each 20 mL)

Acetaminophen 650 mg

Diphenhydramine HCl 25 mg

Phenylephrine HCl 10 mg

Purposes for Day Time

Cough suppressant

Expectorant

Nasal decongestant

Purpose for Night Time

Pain reliever/fever reducer

Antihistamine/Cough suppressant

Nasal decongestant

Uses

Daytime

- helps loosen phlegm (mucus) and thin bronchial secretions to rid the bronchial passageways of bothersome mucus and make coughs more productive
- temporarily relieves
  - cough due to minor throat and bronchial irritation as may occur with the common cold or inhaled irritant
  - the intensity of coughing
  - the impulse to cough to help you get to sleep
  - nasal congestion due to a cold

Nighttime

- temporarily relievesthese common cold and flu symptoms
  - cough
  - nasal congestion
  - minor aches and pains
  - sore throat
  - headache
  - runny nose
  - sneezing
  - temporarily reduces fever
  - controls cough to help you get to sleep

Warnings

Nighttime

Liver warning :

This product contains acetaminophen. Severe liver damage may occur if you take

- more than 4,000 mg of acetaminophen in 24 hours
- with other drugs containing acetaminophen
- 3 or more alcoholic drinks every day while using this product.

Allergy alert:

Acetaminophen may cause severe skin reactions. Symptoms may include:

- skin reddening
- blisters
- rash.

If a skin reaction occurs, stop use and seek medical help right away

Sore throat warning:

If sore throat is severe, persists for more than 2 days, is accompanied or followed by fever, headache, rash, nausea, or vomiting, consult a doctor promptly.

Do not use

Daytime

- if you are taking a prescription monoamine oxidase inhibitor (MAOI) (certan drugs for depression, psychiatric or emotional conditions, or Parkinson's disease), or for 2 weeks after stopping the MAOI drug. If you do not know if your prescription drug contains an MAOI, ask a doctor or pharmacist before taking this product.
- for children under 12 years of age

Nighttime

- With any other drug containing acetaminophen (prescription or nonprescription). If you are not sure whether a drug contains acetaminophen, ask a doctor or pharmacist.
- with any other drug containing diphenhydramine, even one used on the skin
- if you are taking a prescription monoamine oxidase inhibitor (MAOI) (certan drugs for depression, psychiatric or emotional conditions, or Parkinson's disease), or for 2 weeks after stopping the MAOI drug. If you do not know if your prescription drug contains an MAOI, ask a doctor or pharmacist before taking this product
- for children under 12 years of age

Ask a doctor before use if you have

Daytime

- heart disease
- high blood pressure
- thyroid disease
- diabetes
- trouble urinating due to an enlarged prostate gland
- persistent or chronic cough such as occurs with smoking, asthma, chronic bronchitis, emphysema
- cough that occurs with too much phlegm (mucus)

Nighttime

- liver disease
- heart disease
- high blood pressure
- thyroid disease
- diabetes
- glaucoma
- trouble urinating due to an enlarged prostate gland
- a breathing problem such as emphysema or chronic bronchitis
- persistent or chronic cough such as occurs with smoking, asthma, chronic bronchitis, or emphysema
- cough that occurs with too much phlegm (mucus)

Ask a doctor or pharmacist before use if

Nighttime

- you are taking the blood thinning drug warfain
- you are taking sedatives or tranquilizers

When using this product

Daytime

do not use more than directed.

Nighttime

- do not use more than directed
- excitability may occur, especially in children
- marked drowsinessmay occur
- alcohol, sedative, and tranquilizers may increase drowsiness
- avoid alcohol drinks
- be careful when driving a motor vehicle or operating machinery

Stop use and ask a doctor if

Daytime

- nervousness, dizziness or sleeplessness occur
- symptoms do not get better within 7 days or occur with fever
- cough comes back, or occurs with fever, rash, or headache that lasts.

These could be signs of a serious condition.

Nighttime

- nervousness, dizziness, or sleeplessness occur
- pain, nasal congestion, or cough gets worse, or lasts more than 7 days
- fever gets worse, or last more than 3 days
- redness or swelling is present
- new symptoms occur
- cough comes back, or occurs with fever, rash, or headache that lasts.

These could be signs of a serious condition.

If pregnant or breast-feeding,

Daytime

ask a health professional before use

Nighttime

ask a health professional before use

Keep out of reach of children.

Daytime

In case of overdose, get medical help or contact a Poison Control Center (1-800-222-1222) right away.

Nighttime

Overdose warning: Taking more than the recommended dose (overdose) may cause liver damage. In case of overdose, get medical help or contact a Poison Control Center (1-800-222-1222) right away. Quick medical attention is critical for adult as well as for children even if you do not notice any signs or symptoms

Directions

Daytime

- do not take more than 6 doses in any 24-hour period
- measure only with dosing cup provided. Do not use any other dosing device
- keep dosing cup with product
- mL= milliliter
- shake well before using
- adult and children 12 years of age and older: 20 mL in dosing cup provided avery 4 hours
- Children under 12 years of age do not use

Nighttime

- do not take more than directed (see overdose warning)
- do not take more than 6 doses in any24-hour period
- measure only with dosing cup provided. Do not use any other dosing device
- keep dosing cup with product
- mL= milliliter
- dose as follows or as directed by a doctor
- adult and children 12 years and older: 20 mL every 4 hours while symptoms last
- children under 12 years of age: do not use

Other information

Daytime

- each 20 mL contains: sodium 17 mg
- store at 20-25ºC (68-77ºF). Do not refrigerate.

Nighttime

- each 20 mL contains: sodium 10 mg
- store at 20-25ºC (68-77ºF). Do not refrigerate

Inactive ingredients

Inactive ingredients for Day Time

citric acid, disodium EDTA, FD&C blue #1 FD&C red #40, flavor, glycerin, propyl gallate, propylene glycol, purified water, sodium benzoate, sodium citrate, sorbitol, sucralose,xanthan gum

Inactive ingredients for Night Time

citric acid, EDTA disodium, FD&C blue #1, Fd&C red #40, flavor, glycerin, propylene gallate, propylene glycol, purified water, sodium benzoate, sodium citrate, sorbitol, sucralose, xanthan gum

Principal Display Panel

DAYTIME

Severe Cough & Congestion

DEXTROMETHORPHAN HBr - Cough Suppressant

GUAIFENESIN - Expectorant

PHENYLEPHRINE HCI - Nasal Decongestant

MAXIMUM STRENGTH

Multi-Symptom

- Relieves nasal & chest congestion
- Soothes Cough
- Thins & loosen mucus

For ages 12 & over

FL OZ (mL)

Compare to the active ingredients in Maximum Strength Mucinex®FAST-MAX® Severe Congestion & Cough and Nighttime Cold & Flu*

TAMPER EVIDENT: DO NOT USE IF PRINTED SAFETY SEAL AROUND OR UNDER CAP IS BROKEN OR MISSING

*This product is not manufactured or distributed by Reckitt Benckiser, distributor of Maximum Strength Mucinex® FAST-MAX® Severe Congestion & Cough & Nighttime Cold & Flu

NIGHTTIME

Cold & FLU

ACETAMINOPHEN - Pain Reliever ; Fever Reducer

DIPHENHYDRAMINE HCl - Antihistamine / Cough Suppressant

PHENYLEPHRINE HCl / Nasal Decongestant

MAXIMUM STRENGTH

Multi-Strength

- Relieves headache & fever
- Controls cough
- Relieves nasal congestion
- Relieves runny nose & sneezing

For ages 12 & over

FL OZ (mL)

Distributed by: CVS Pharmacy, Inc.

One CVS Drive, Woonsocket, RI 02895

CVS.com

Product Label

CVS HEALTH Severe Cough & Congestion Nighttime Cold & Flu